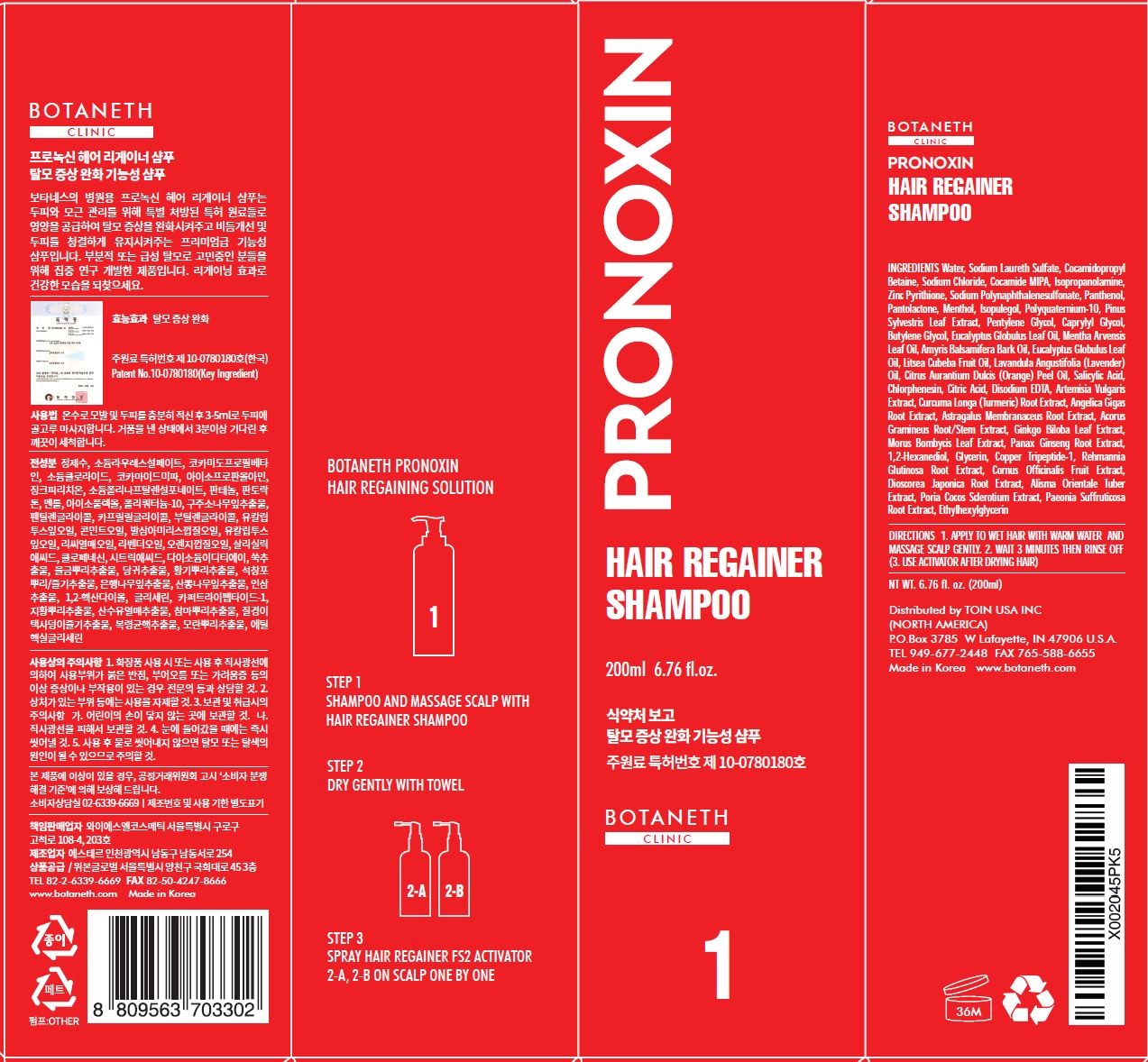 DRUG LABEL: BOTANETH PRONOXIN HAIR REGAINER
NDC: 73199-0001 | Form: SHAMPOO
Manufacturer: OUIBON GLOBAL
Category: otc | Type: HUMAN OTC DRUG LABEL
Date: 20190713

ACTIVE INGREDIENTS: SALICYLIC ACID 0.2 g/100 mL; PYRITHIONE ZINC 0.3 g/100 mL
INACTIVE INGREDIENTS: WATER

Drug Facts

ACTIVE INGREDIENT

zinc pyrithione, salicylic acid

INACTIVE INGREDIENT

Water, Sodium Laureth Sulfate, Cocamidopropyl Betaine, Sodium Chloride, Cocamide MIPA, Isopropanolamine, Zinc Pyrithione, Sodium Polynaphthalenesulfonate, Panthenol, Pantolactone, Menthol, Isopulegol, Polyquaternium-10, Pinus Sylvestris Leaf Extract, Pentylene Glycol, Caprylyl Glycol, Butylene Glycol, Eucalyptus Globulus Leaf Oil, Mentha Arvensis Leaf Oil, Amyris Balsamifera Bark Oil, Eucalyptus Globulus Leaf Oil, Litsea Cubeba Fruit Oil, Lavandula Angustifolia (Lavender) Oil, Citrus Aurantium Dulcis (Orange) Peel Oil, Salicylic Acid, Chlorphenesin, Citric Acid, Disodium EDTA, Artemisia Vulgaris Extract, Curcuma Longa (Turmeric) Root Extract, Angelica Gigas Root Extract, Astragalus Membranaceus Root Extract, Acorus Gramineus Root/Stem Extract, Ginkgo Biloba Leaf Extract, Morus Bombycis Leaf Extract, Panax Ginseng Root Extract, 1,2-Hexanediol, Glycerin, Copper Tripeptide-1, Rehmannia Glutinosa Root Extract, Cornus Officinalis Fruit Extract, Dioscorea Japonica Root Extract, Alisma Orientale Tuber Extract, Poria Cocos Sclerotium Extract, Paeonia Suffruticosa Root Extract, Ethylhexylglycerin

PURPOSE

Protect scalp, hair loss prevention

keep out of reach of the children

INDICATIONS AND USAGE

1. APPLY TO WET HAIR WITH WARM WATER AND MASSAGE SCALP GENTLY.

2. WAIT 3 MINUTES THEN RINSE OFF (3. USE ACTIVATOR AFTER DRYING HAIR)

WARNINGS

1. In case of using cosmetics or after use, please consult a specialist if there is any abnormal symptom or side effect such as red spot, swelling or itching in direct sunlight.
2. Do not use on wounded areas.
3. In case of contact with eyes, wash immediately.
4. Care should be taken not to rinse with water after use, as it may cause hair loss or discoloration.

DOSAGE AND ADMINISTRATION

for topical use only